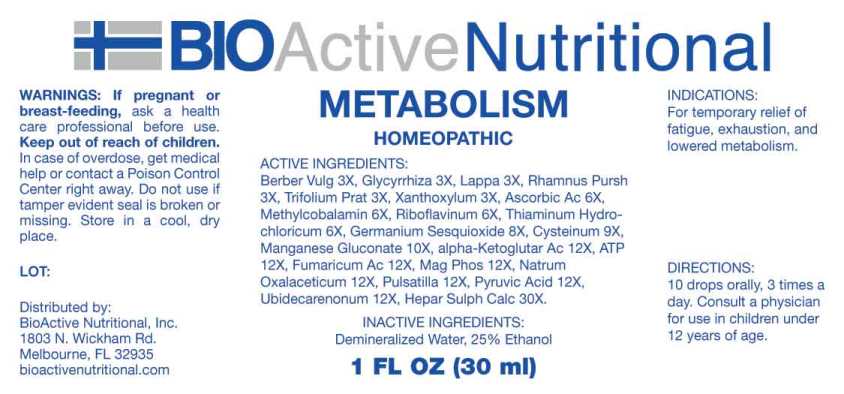 DRUG LABEL: Metabolism
NDC: 43857-0587 | Form: LIQUID
Manufacturer: BioActive Nutritional, Inc.
Category: homeopathic | Type: HUMAN OTC DRUG LABEL
Date: 20241017

ACTIVE INGREDIENTS: BERBERIS VULGARIS ROOT BARK 3 [hp_X]/1 mL; GLYCYRRHIZA GLABRA 3 [hp_X]/1 mL; ARCTIUM LAPPA ROOT 3 [hp_X]/1 mL; FRANGULA PURSHIANA BARK 3 [hp_X]/1 mL; TRIFOLIUM PRATENSE FLOWER 3 [hp_X]/1 mL; ZANTHOXYLUM AMERICANUM BARK 3 [hp_X]/1 mL; ASCORBIC ACID 6 [hp_X]/1 mL; METHYLCOBALAMIN 6 [hp_X]/1 mL; RIBOFLAVIN 6 [hp_X]/1 mL; THIAMINE HYDROCHLORIDE 6 [hp_X]/1 mL; GERMANIUM SESQUIOXIDE 8 [hp_X]/1 mL; CYSTEINE 9 [hp_X]/1 mL; MANGANESE GLUCONATE 10 [hp_X]/1 mL; ADENOSINE TRIPHOSPHATE DISODIUM 12 [hp_X]/1 mL; .ALPHA.-KETOGLUTARIC ACID 12 [hp_X]/1 mL; FUMARIC ACID 12 [hp_X]/1 mL; MAGNESIUM PHOSPHATE, DIBASIC TRIHYDRATE 12 [hp_X]/1 mL; SODIUM DIETHYL OXALACETATE 12 [hp_X]/1 mL; PULSATILLA VULGARIS WHOLE 12 [hp_X]/1 mL; PYRUVIC ACID 12 [hp_X]/1 mL; UBIDECARENONE 12 [hp_X]/1 mL; CALCIUM SULFIDE 30 [hp_X]/1 mL
INACTIVE INGREDIENTS: WATER; ALCOHOL

DRUG FACTS:

ACTIVE INGREDIENTS:

Berberis Vulgaris 3X, Glycyrrhiza Glabra 3X, Lappa Major 3X, Rhamnus Purshiana 3X, Trifolium Pratense 3X, Xanthoxylum Fraxineum 3X, Ascorbic Acid 6X, Methylcobalamin 6X, Riboflavinum 6X, Thiaminum Hydrochloricum 6X, Germanium Sesquioxide 8X, Cysteinum 9X, Manganese Gluconate 10X, Adenosinum Triphosphoricum Dinatrum 12X, Alpha-Ketoglutaricum Acidum 12X, Fumaricum Acidum 12X, Magnesia Phosphorica 12X, Natrum Oxalaceticum 12X, Pulsatilla (Vulgaris) 12X, Pyruvic Acid 12X, Ubidecarenonum 12X, Hepar Sulphuris Calcareum 30X.

INDICATIONS:

For temporary relief of fatigue, exhaustion, and lowered metabolism.

WARNINGS:

If pregnant or breast-feeding, ask a health care professional before use.

Keep out of reach of children. In case of overdose, get medical help or contact a Poison Control Center right away.

Do not use if tamper evident seal is broken or missing.

Store in a cool, dry place.

Keep out of reach of children. In case of overdose, get medical help or contact a Poison Control Center right away.

DIRECTIONS:

10 drops orally, 3 times a day. Consult a physician for use in children under 12 years of age.

INDICATIONS:

For temporary relief of fatigue, exhaustion, and lowered metabolism.

INACTIVE INGREDIENTS:

Demineralized Water, 25% Ethanol

QUESTIONS:

Distributed by:

BioActive Nutritional, Inc.

1803 N. Wickham Rd.

Melbourne, FL 32935

bioactivenutritional.com

PACKAGE DISPLAY LABEL:

BIOActive Nutritional

METABOLISM

HOMEOPATHIC

1 FL OZ (30 ml)